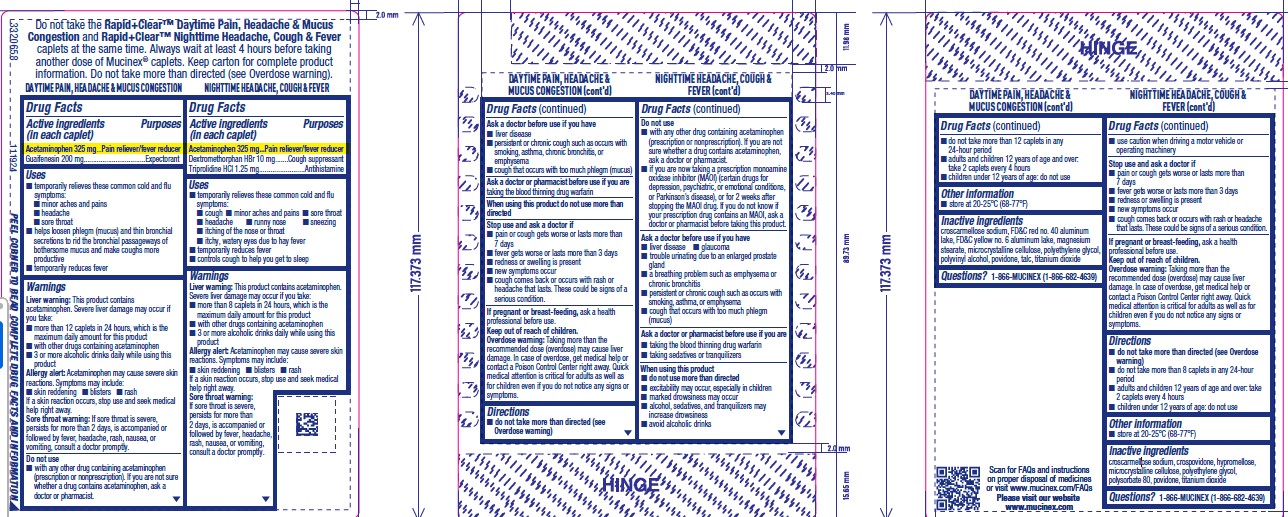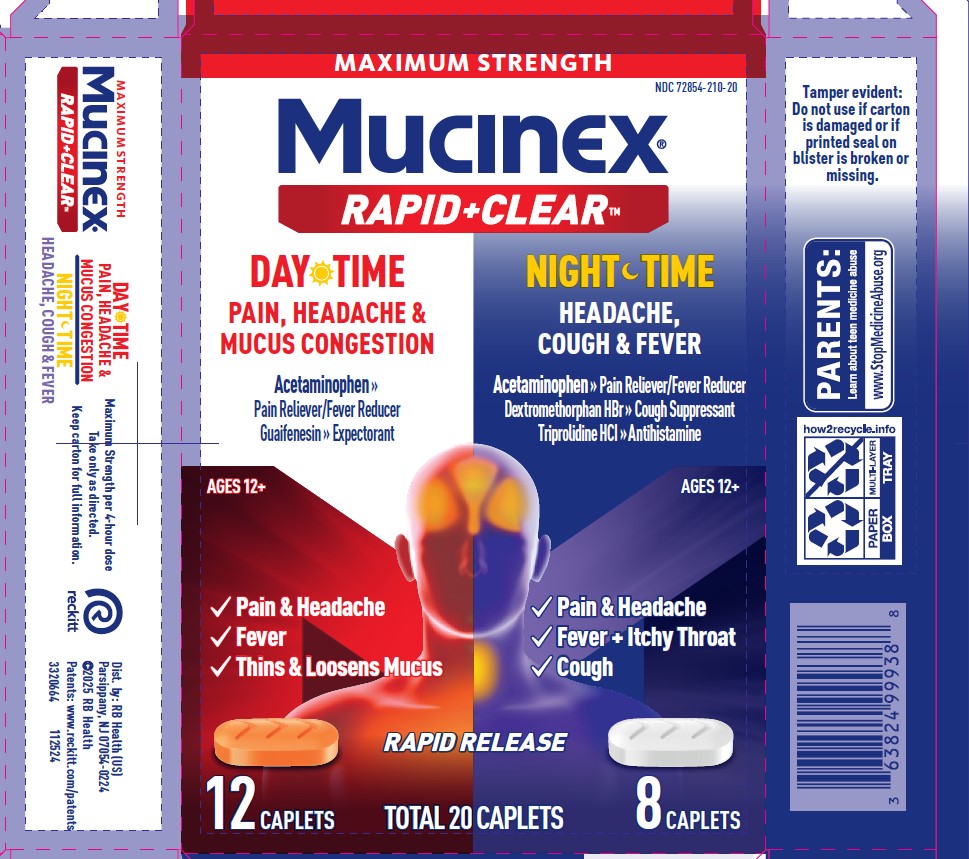 DRUG LABEL: MUCINEX DAY TIME PAIN, HEADACHE and MUCUS CONGESTION and MUCINEX NIGHT TIME HEADACHE, COUGH and FEVER
NDC: 72854-210 | Form: KIT | Route: ORAL
Manufacturer: RB Health (US) LLC
Category: otc | Type: HUMAN OTC DRUG LABEL
Date: 20250602

ACTIVE INGREDIENTS: ACETAMINOPHEN 325 mg/1 1; GUAIFENESIN 200 mg/1 1; ACETAMINOPHEN 325 mg/1 1; DEXTROMETHORPHAN HYDROBROMIDE 10 mg/1 1; TRIPROLIDINE HYDROCHLORIDE 1.25 mg/1 1
INACTIVE INGREDIENTS: CROSCARMELLOSE SODIUM; FD&C RED NO. 40; FD&C YELLOW NO. 6; ALUMINUM OXIDE; MAGNESIUM STEARATE; MICROCRYSTALLINE CELLULOSE; POLYETHYLENE GLYCOL, UNSPECIFIED; POLYVINYL ALCOHOL, UNSPECIFIED; POVIDONE, UNSPECIFIED; TALC; TITANIUM DIOXIDE; HYPROMELLOSE, UNSPECIFIED; POLYETHYLENE GLYCOL, UNSPECIFIED; CROSCARMELLOSE SODIUM; CROSPOVIDONE; MICROCRYSTALLINE CELLULOSE; POVIDONE, UNSPECIFIED; TITANIUM DIOXIDE; POLYSORBATE 80

MUCINEX® Rapid Clear® Pain, Headache & Mucus Congestion and Nighttime Caplets

Drug Facts

ACTIVE INGREDIENT

Acetaminophen 325 mg
Guaifenesin 200 mg

Mucinex Nightshift Night Sinus Purposes
Acetaminophen 325 mg Pain reliever/fever reducer
Dextromethorphan HBr 10 mg Cough suppressant
Triprolidine HCl 1.25 mg Antihistamine

PURPOSE

Active ingredients (in each caplet) Mucinex Sinus-Max Day Pressure, Pain & Cough | Purposes
Acetaminophen 325 mg | Pain reliever
Guaifenesin 200 mg | Expectorant

Active ingredients (in each caplet) Mucinex Nightshift Night Sinus | Purposes
Acetaminophen 325 mg | Pain reliever/fever reducer
Dextromethorphan HBr 10 mg | Cough suppressant
Triprolidine HCl 1.25 mg | Antihistamine

Uses

Mucinex Sinus-Max Day Pressure, Pain & Cough

- temporarily relieves:
  - nasal congestion
  - headache
  - minor aches and pains
  - cough
  - sinus congestion and pressure
- temporarily promotes nasal and/or sinus drainage
- helps loosen phlegm (mucus) and thin bronchial secretions to rid the bronchial passageways of bothersome mucus and make coughs more productive

Mucinex Nightshift Night Sinus

- temporarily relieves these common cold and flu symptoms:
  - cough
  - nasal congestion
  - minor aches and pains
  - sore throat
  - headache
  - sneezing
  - sinus congestion and pressure
  - runny nose
  - itching of the nose or throat
  - itchy, watery eyes due to hay fever
- temporarily reduces fever
- controls cough to help you get to sleep

Warnings

Liver warning

This product contains acetaminophen.

Severe liver damage may occur if you take:

- more than 4,000 mg in 24 hours, which is the maximum daily amount
- with other drugs containing acetaminophen
- 3 or more alcoholic drinks daily while using this product

Allergy alert

Acetaminophen may cause severe skin reactions. Symptoms may include:

- skin reddening
- blisters
- rash

If a skin reaction occurs, stop use and seek medical help right away.

Sore throat warning (Nightshift Night Sinus only)

If sore throat is severe, persists for more than 2 days, is accompanied or followed by fever, headache, rash, nausea, or vomiting, consult a doctor promptly.

Do not use

- with any other drug containing acetaminophen (prescription or nonprescription). If you are not sure whether a drug contains acetaminophen, ask a doctor or pharmacist.
- if you are now taking a prescription monoamine oxidase inhibitor (MAOI) (certain drugs for depression, psychiatric, or emotional conditions, or Parkinson's disease), or for 2 weeks after stopping the MAOI drug. If you do not know if your prescription drug contains an MAOI, ask a doctor or pharmacist before taking this product.

Ask a doctor before use if you have

- liver disease
- heart disease
- diabetes
- high blood pressure
- thyroid disease
- glaucoma (Nightshift Night Sinus only)
- trouble urinating due to an enlarged prostate gland
- a breathing problem such as emphysema or chronic bronchitis (Nightshift Night Sinus only)
- persistent or chronic cough such as occurs with smoking, asthma, chronic bronchitis, or emphysema
- cough that occurs with too much phlegm (mucus)

Ask a doctor or pharmacist before use if you are

- taking the blood thinning drug warfarin
- taking sedatives or tranquilizers (Nightshift Night Sinus only)

When using this product

- do not use more than directed
- excitability may occur, especially in children (Nightshift Night Sinus only)
- marked drowsiness may occur (Nightshift Night Sinus only)
- alcohol, sedatives, and tranquilizers may increase drowsiness (Nightshift Night Sinus only)
- avoid alcoholic drinks (Nightshift Night Sinus only)
- use caution when driving a motor vehicle or operating machinery (Nightshift Night Sinus only)

Stop use and ask a doctor if

- nervousness, dizziness, or sleeplessness occur
- pain, nasal congestion, or cough gets worse or lasts more than 7 days
- fever gets worse or lasts more than 3 days
- redness or swelling is present
- new symptoms occur
- cough comes back, or occurs with fever, rash, or headache that lasts. These could be signs of a serious condition.

PREGNANCY OR BREAST FEEDING

If pregnant or breast-feeding, ask a health professional before use.

Keep out of reach of children.

Overdose warning

Taking more than the recommended dose (overdose) may cause liver damage. In case of overdose, get medical help or contact a Poison Control Center right away. Quick medical attention is critical for adults as well as for children even if you do not notice any signs or symptoms.

Directions

Mucinex Sinus-Max Day Pressure, Pain & Cough

- do not take more than directed (see Overdose warning)
- do not take more than 12 caplets in any 24-hour period
- adults and children 12 years of age and over: take 2 caplets every 4 hours
- children under 12 years of age: do not use

Mucinex Nightshift Night Sinus

- do not take more than directed (see Overdose warning)
- do not take more than 8 caplets in any 24-hour period
- adults and children 12 years of age and over: take 2 caplets every 4 hours
- children under 12 years of age: do not use

Other information

- store at 20-25°C (68-77°F)

Inactive ingredients

Mucinex Sinus-Max Day Pressure, Pain & Cough

croscarmellose sodium, FD&C red no. 40 aluminum
lake, FD&C yellow no. 6 aluminum lake, magnesium
stearate, microcrystalline cellulose, polyethylene glycol,
polyvinyl alcohol, povidone, talc, titanium dioxide

Mucinex Nightshift Night Sinus

croscarmellose sodium, crospovidone, hypromellose,
microcrystalline cellulose, polyethylene glycol,
polysorbate 80, povidone, titanium dioxide

Questions? 1-866-MUCINEX (1-866-682-4639)

You may also report side effects to this phone number.

Dist. by: RB Health (US)
Parsippany, NJ 07054-0224

PRINCIPAL DISPLAY PANEL - Kit Carton

NDC 72854-210